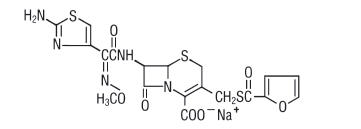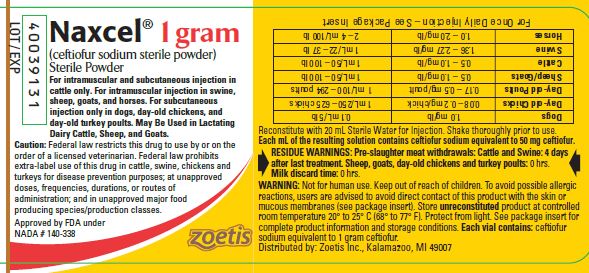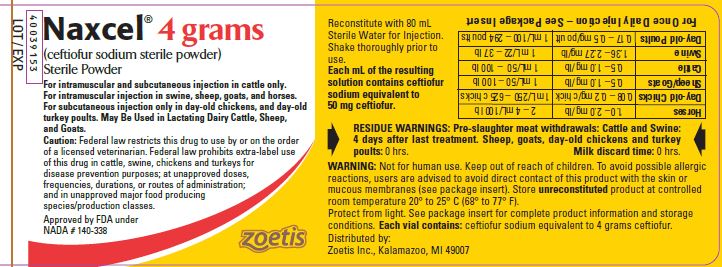 DRUG LABEL: Naxcel
NDC: 54771-3362 | Form: POWDER
Manufacturer: Zoetis Inc.
Category: animal | Type: PRESCRIPTION ANIMAL DRUG LABEL
Date: 20230725

ACTIVE INGREDIENTS: CEFTIOFUR SODIUM 1000 mg/1 g

Naxcel®

Naxcel®

brand of ceftiofur sodium
sterile powder

For intramuscular and subcutaneous injection in cattle only. For intramuscular injection in swine, sheep, goats, and horses. For subcutaneous injection only in dogs, day-old chickens and day-old turkey poults. This product may be used in lactating dairy cattle, sheep, and goats.

CAUTION

Federal law restricts this drug to use by or on the order of a licensed veterinarian. Federal law prohibits extra-label use of this drug in cattle, swine, chickens and turkeys for disease prevention purposes; at unapproved doses, frequencies, durations, or routes of administration; and in unapproved major food producing species/production classes.

DESCRIPTION

NAXCEL Sterile Powder contains the sodium salt of ceftiofur which is a broad spectrum cephalosporin antibiotic active against gram-positive and gram-negative bacteria including β-lactamase-producing strains. Like other cephalosporins, ceftiofur is bactericidal in vitro, resulting from inhibition of cell wall synthesis.

Each mL of the reconstituted drug contains ceftiofur sodium equivalent to 50 mg ceftiofur. The pH was adjusted with sodium hydroxide and monobasic potassium phosphate.

Chemical Structure of Ceftiofur Sodium

Chemical Name of Ceftiofur Sodium

5-Thia-1-azabicyclo[4.2.0]oct-2-ene-2-carboxylic acid, 7-[[(2-amino-4-thiazolyl)(methoxyimino)-acetyl]amino]-3-[[(2-furanylcarbonyl)thio] methyl]-8-oxo-, monosodium salt, [6R-[6α,7β(Z)]]-

RECONSTITUTION OF THE STERILE POWDER

NAXCEL Sterile Powder should be reconstituted as follows:

- 1 gram vial—Reconstitute with 20 mL Sterile Water for Injection. Each mL of the resulting solution contains ceftiofur sodium equivalent to 50 mg ceftiofur.
- 4 gram vial—Reconstitute with 80 mL Sterile Water for Injection. Each mL of the resulting solution contains ceftiofur sodium equivalent to 50 mg ceftiofur.
- Shake thoroughly prior to use.

INDICATIONS

Cattle

NAXCEL Sterile Powder is indicated for treatment of bovine respiratory disease (shipping fever, pneumonia) associated with Mannheimia haemolytica, Pasteurella multocida and Histophilus somni. NAXCEL Sterile Powder is also indicated for treatment of acute bovine interdigital necrobacillosis (foot rot, pododermatitis) associated with Fusobacterium necrophorum and Bacteroides melaninogenicus.

Swine

NAXCEL Sterile Powder is indicated for treatment/control of swine bacterial respiratory disease (swine bacterial pneumonia) associated with Actinobacillus (Haemophilus) pleuropneumoniae, Pasteurella multocida, Salmonella choleraesuis and Streptococcus suis.

Sheep

NAXCEL Sterile Powder is indicated for treatment of sheep respiratory disease (sheep pneumonia) associated with Mannheimia haemolytica and Pasteurella multocida.

Goats

NAXCEL Sterile Powder is indicated for treatment of caprine respiratory disease (goat pneumonia) associated with Mannheimia haemolytica and Pasteurella multocida.

Horses

NAXCEL Sterile Powder is indicated for treatment of respiratory infections in horses associated with Streptococcus zooepidemicus.

Dogs

NAXCEL Sterile Powder is indicated for the treatment of canine urinary tract infections associated with Escherichia coli and Proteus mirabilis.

Day-Old Chicks

NAXCEL Sterile Powder is indicated for the control of early mortality, associated with E. coli organisms susceptible to ceftiofur, in day-old chicks.

Day-Old Turkey Poults

NAXCEL Sterile Powder is indicated for the control of early mortality, associated with E. coli organisms susceptible to ceftiofur, in day-old turkey poults.

DOSAGE AND ADMINISTRATION

Cattle

Administer to cattle by intramuscular or subcutaneous injection at the dosage of 0.5 to 1.0 mg ceftiofur per pound (1.1 to 2.2 mg/kg) of body weight (1-2 mL reconstituted sterile solution per 100 lbs body weight). Treatment should be repeated at 24-hour intervals for a total of three consecutive days. Additional treatments may be given on days four and five for animals which do not show a satisfactory response (not recovered) after the initial three treatments. Selection of dosage (0.5 to 1.0 mg/lb) should be based on the practitioner's judgement of severity of disease (i.e., for respiratory disease, extent of elevated body temperature, depressed physical appearance, increased respiratory rate, coughing and/or loss of appetite; and for foot rot, extent of swelling, lesion and severity of lameness).

Swine

Administer to swine by intramuscular injection at the dosage of 1.36 to 2.27 mg ceftiofur per pound (3.0 to 5.0 mg/kg) of body weight (1 mL of reconstituted sterile solution per 22 to 37 lbs body weight). Treatment should be repeated at 24-hour intervals for a total of three consecutive days.

Sheep

Administer to sheep by intramuscular injection at the dosage of 0.5 to 1.0 mg ceftiofur per pound (1.1 to 2.2 mg/kg) of body weight (1-2 mL reconstituted sterile solution per 100 lbs body weight). Treatment should be repeated at 24-hour intervals for a total of three consecutive days. Additional treatments may be given on days four and five for animals which do not show a satisfactory response (not recovered) after the initial three treatments. Selection of dosage (0.5 to 1.0 mg/lb) should be based on the practitioner's judgement of severity of disease (i.e., extent of elevated body temperature, depressed physical appearance, increased respiratory rate, coughing and/or loss of appetite).

Goats

Administer to goats by intramuscular injection at the dosage of 0.5 to 1.0 mg ceftiofur per pound (1.1 to 2.2 mg/kg) of body weight (1-2 mL reconstituted sterile solution per 100 lbs body weight). Treatment should be repeated at 24‑hour intervals for a total of three consecutive days. Additional treatments may be given on days four and five for animals which do not show a satisfactory response (not recovered) after the initial three treatments. Selection of dosage (0.5 to 1.0 mg/lb) should be based on the practitioner's judgement of severity of disease (i.e., extent of elevated body temperature, depressed physical appearance, increased respiratory rate, coughing and/or loss of appetite). Pharmacokinetic data indicate that elimination of the drug is more rapid in lactating does. For lactating does, the high end of the dose range is recommended.

Horses

Administer to horses by intramuscular injection at the dosage of 1.0 to 2.0 mg ceftiofur per pound (2.2 to 4.4 mg/kg) of body weight (2-4 mL reconstituted sterile solution per 100 lbs body weight). A maximum of 10 mL may be administered per injection site. Treatment should be repeated at 24-hour intervals, continued for 48 hours after clinical signs have disappeared and should not exceed 10 days.

Dogs

Administer to dogs by subcutaneous injection at the dosage of 1.0 mg ceftiofur per pound (2.2 mg/kg) of body weight (0.1 mL reconstituted sterile solution per 5 lbs body weight). Treatment should be repeated at 24-hour intervals for 5-14 days.

Reconstituted NAXCEL Sterile Powder is to be administered to dogs by subcutaneous injection. No vial closure should be entered more than 20 times. Therefore, only the 1 gram vial is approved for use in dogs.

Day-Old Chicks

Administer by subcutaneous injection in the neck region of day-old chicks at the dosage of 0.08 to 0.20 mg ceftiofur/chick. One mL of the 50 mg/mL reconstituted solution will treat approximately 250 to 625 day-old chicks.

Reconstituted NAXCEL Sterile Powder is to be administered by subcutaneous injection only. A sterile 26 gauge needle and syringe or properly cleaned automatic injection machine should be used.

Day-Old Turkey Poults

Administer by subcutaneous injection in the neck region of day-old turkey poults at the dosage of 0.17 to 0.5 mg ceftiofur/poult. One mL of the 50 mg/mL reconstituted solution will treat approximately 100 to 294 day-old turkey poults.

Reconstituted NAXCEL Sterile Powder is to be administered by subcutaneous injection only.

CONTRAINDICATIONS

As with all drugs, the use of NAXCEL Sterile Powder is contraindicated in animals previously found to be hypersensitive to the drug.

WARNINGS

NOT FOR HUMAN USE. KEEP OUT OF REACH OF CHILDREN.

Penicillins and cephalosporins can cause allergic reactions in sensitized individuals. Topical exposures to such antimicrobials, including ceftiofur, may elicit mild to severe allergic reactions in some individuals. Repeated or prolonged exposure may lead to sensitization. Avoid direct contact of the product with the skin, eyes, mouth, and clothing.

Persons with a known hypersensitivity to penicillin or cephalosporins should avoid exposure to this product.

In case of accidental eye exposure, flush with water for 15 minutes. In case of accidental skin exposure, wash with soap and water. Remove contaminated clothing. If allergic reaction occurs (e.g., skin rash, hives, difficult breathing), seek medical attention.

CONTACT INFORMATION

For a copy of the Safety Data Sheet or to report adverse reactions, call Zoetis Inc. at 1-888-963-8471. For additional information about adverse drug experience reporting for animal drugs, contact FDA at 1-888-FDA-VETS or www.fda.gov/reportanimalae.

RESIDUE WARNINGS:

Cattle: When used according to label indications, dosage and routes of administration, treated cattle must not be slaughtered for 4 days following the last treatment. When used according to label indications, dosage and routes of administration, a milk discard time is not required. Use of dosages in excess of those indicated or by unapproved routes of administration, such as intramammary, may result in illegal residues in edible tissues and/or in milk.

Swine: When used according to label indications, dosage and route of administration, treated pigs must not be slaughtered for 4 days following the last treatment. Use of dosages in excess of those indicated or by unapproved routes of administration may result in illegal residues in edible tissues.

Sheep: Neither a pre-slaughter drug withdrawal interval nor a milk discard time is required when this product is used according to label indications, dosage, and route of administration. Use of dosages in excess of those indicated or by unapproved routes of administration, such as intramammary, may result in illegal residues in edible tissues and/or in milk.

Goats: Neither a pre-slaughter drug withdrawal interval nor a milk discard time is required when this product is used according to label indications, dosage, and route of administration. Use of dosages in excess of those indicated or by unapproved routes of administration, such as intramammary, may result in illegal residues in edible tissues and/or in milk.

Horses: Do not use in horses intended for human consumption.

PRECAUTIONS

The effects of ceftiofur on the reproductive performance, pregnancy, and lactation of cattle, swine, sheep, and goats have not been determined.

Cattle

Following subcutaneous administration of ceftiofur sodium in the neck, small areas of discoloration at the site may persist beyond five days, potentially resulting in trim loss of edible tissues at slaughter.

As with any parenteral injection, localized post-injection bacterial infections may result in abscess formation. Attention to hygienic procedures can minimize their occurrence.

Swine

The safety of ceftiofur has not been determined for swine intended for breeding.

Horses

The safety of ceftiofur has not been determined for horses intended for breeding. The administration of antimicrobials to horses under conditions of stress may be associated with acute diarrhea that could be fatal. If acute diarrhea is observed, discontinue use of this antimicrobial and initiate appropriate therapy.

Dogs

The safety of ceftiofur has not been determined for dogs intended for breeding, or pregnant dogs.

ADVERSE REACTIONS

The use of ceftiofur may result in some signs of immediate and transient local pain to the animal.

CLINICAL MICROBIOLOGY

Summaries of MIC data are presented in Tables 1 and 2. Testing followed Clinical and Laboratory Standards Institute (CLSI) Guidelines.

Table 1. Ceftiofur MIC Values of Bacterial Isolates from Clinical Field Studies in the USA
Animal | Organism | Number Tested | Date Tested | MIC90 [Minimum inhibitory concentration (MIC) for 90% of the isolates.] (μg/mL) | MIC Range (μg/mL)
Bovine | Mannheimia haemolytica | 461 | 1988-1992 | 0.06 | ≤ 0.03-0.13
Bovine | Mannheimia haemolytica | 42 | 1993 | 0.015 | ≤ 0.003-0.03
Bovine | Pasteurella multocida | 318 | 1988-1992 | 0.06 | ≤ 0.03-0.25
Bovine | Pasteurella multocida | 48 | 1993 | ≤ 0.003 | ≤ 0.003-0.015
Bovine | Histophilus somni | 109 | 1988-1992 | 0.06 | ≤ 0.03-0.13
Bovine | Histophilus somni | 59 | 1993 | ≤ 0.0019 | no range
Bovine | Fusobacterium necrophorum | 17 | 1994 | ≤ 0.06 | no range
Swine | Actinobacillus pleuropn. | 83 | 1993 | ≤ 0.03 | ≤ 0.03-0.06
Swine | Pasteurella multocida | 74 | 1993 | ≤ 0.03 | ≤ 0.03-0.06
Swine | Streptococcus suis | 94 | 1993 | 0.25 | ≤ 0.03-1.0
Swine | Salmonella choleraesuis | 50 | 1993 | 1.0 | 1.0-2.0
Swine | beta-hemolytic Streptococcus spp. | 24 | 1993 | ≤ 0.03 | ≤ 0.03-0.06
Swine | Actinobacillus suis | 77 | 1998 | 0.0078 | 0.0019-0.0078
Swine | Haemophilus parasuis | 76 | 1998 | 0.06 | 0.0039-0.25
Sheep | Mannheimia haemolytica | 39 | 1992 | 0.13 | ≤ 0.03-0.13
Sheep | Pasteurella multocida | 23 | 1992 | ≤ 0.03 | no range
Canine | Escherichia coli | 44 | 1992 | 4.0 | 0.06-64.0
Canine | Escherichia coli | 18 | 1990 | 0.25 | 0.13-0.5
Canine | Proteus mirabilis | 17 | 1990 | ≤ 0.06 | ≤ 0.06-0.5
Canine | Proteus mirabilis | 23 | 1992 | 1.0 | ≤ 0.06-4.0
Turkey | Escherichia coli | 1204 | 1995 | 1.0 | 0.13->32.0

Table 2. Ceftiofur MIC Values of Bacterial Isolates from Diagnostic Laboratories in the USA and Canada [The following in vitro data are available but their clinical significance is unknown.]
Animal | Organism | Number Tested | Date Tested | MIC90 [Minimum inhibitory concentration (MIC) for 90% of the isolates.] (μg/mL) | MIC Range (μg/mL)
Bovine | Mannheimia haemolytica | 110 | 1997-1998 | 0.06 | ≤ 0.03-0.25
Bovine | Mannheimia haemolytica | 139 | 1998-1999 | ≤ 0.03 | ≤ 0.03-0.5
Bovine | Mannheimia haemolytica | 209 | 1999-2000 | ≤ 0.03 | ≤ 0.03-0.12
Bovine | Mannheimia haemolytica | 189 | 2000-2001 | ≤ 0.03 | ≤ 0.03-0.12
Bovine | Pasteurella multocida | 107 | 1997-1998 | ≤ 0.03 | ≤ 0.03-0.25
Bovine | Pasteurella multocida | 181 | 1998-1999 | ≤ 0.03 | ≤ 0.03-0.5
Bovine | Pasteurella multocida | 208 | 1999-2000 | ≤ 0.03 | ≤ 0.03-0.12
Bovine | Pasteurella multocida | 259 | 2000-2001 | ≤ 0.03 | ≤ 0.03-0.12
Bovine | Histophilus somni | 48 | 1997-1998 | ≤ 0.03 | ≤ 0.03-0.25
Bovine | Histophilus somni | 87 | 1998-1999 | ≤ 0.03 | ≤ 0.03-0.125
Bovine | Histophilus somni | 77 | 1999-2000 | ≤ 0.03 | ≤ 0.03-0.06
Bovine | Histophilus somni | 129 | 2000-2001 | ≤ 0.03 | ≤ 0.03-0.12
Bovine | Bacteroides fragilis group | 29 | 1994 | 16.0 | ≤ 0.06->16.0
Bovine | Bacteroides spp., non-fragilis group | 12 | 1994 | 16.0 | 0.13->16.0
Bovine | Peptostreptococcus anaerobius | 12 | 1994 | 2.0 | 0.13-2.0
Swine | Actinobacillus pleuropn. | 97 | 1997-1998 | ≤ 0.03 | no range
Swine | Actinobacillus pleuropn. | 111 | 1998-1999 | ≤ 0.03 | ≤ 0.03-0.25
Swine | Actinobacillus pleuropn. | 126 | 1999-2000 | ≤ 0.03 | ≤ 0.03-0.06
Swine | Actinobacillus pleuropn. | 89 | 2000-2001 | ≤ 0.03 | ≤ 0.03-0.06
Swine | Pasteurella multocida | 114 | 1997-1998 | ≤ 0.03 | ≤ 0.03-1.0
Swine | Pasteurella multocida | 147 | 1998-1999 | ≤ 0.03 | ≤ 0.03-0.5
Swine | Pasteurella multocida | 173 | 1999-2000 | ≤ 0.03 | ≤ 0.03-0.06
Swine | Pasteurella multocida | 186 | 2000-2001 | ≤ 0.03 | ≤ 0.03-0.12
Swine | Streptococcus suis | 106 | 1997-1998 | 0.5 | ≤ 0.03-4.0
Swine | Streptococcus suis | 142 | 1998-1999 | 0.25 | ≤ 0.03-1.0
Swine | Streptococcus suis | 146 | 1999-2000 | 0.06 | ≤ 0.03-4.0
Swine | Streptococcus suis | 167 | 2000-2001 | 0.06 | ≤ 0.03-4.0
Swine | Salmonella choleraesuis | 96 | 1999-2000 | 1.0 | 0.03->4.0
Swine | Salmonella choleraesuis | 101 | 2000-2001 | 1.0 | 0.5-2.0
Equine | Streptococcus equi subsp. equi | 12 | 1994 | ≤ 0.0019 | no range
Equine | Streptococcus equi subsp. equi | 29 | 2002 | ≤ 0.03 | ≤ 0.03-0.05
Equine | Streptococcus zooepidemicus | 48 | 1994 | ≤ 0.0019 | no range
Equine | Streptococcus zooepidemicus | 59 | 2002 | ≤ 0.03 | ≤ 0.03-0.25
Equine | Rhodococcus equi | 66 | 1998 | 4.0 | ≤ 0.03-16.0
Equine | Rhodococcus equi | 42 | 2002 | 8.0 | ≤ 0.03->32.0
Equine | Bacteroides fragilis group | 32 | 1995 | >16.0 | 0.13->16.0
Equine | Bacteroides spp., non-fragilis group | 12 | 1995 | 4.0 | 0.25-4.0
Equine | Fusobacterium necrophorum | 16 | 1995 | ≤ 0.06 | no range
Canine | Escherichia coli | 26 | 2000 | 32 | 0.25->32
Canine | Proteus mirabilis | 14 | 2000 | 0.25 | 0.06-0.25
Turkey | Escherichia coli | 17 | 1998-1999 | 1.0 | 0.25-1.0
Turkey | Escherichia coli | 25 | 1999-2000 | 0.50 | 0.12-0.5
Turkey | Escherichia coli | 20 | 2000-2001 | 2.0 | 0.12-16.0
Turkey | Citrobacter spp. | 37 | 1995 | 32.0 | 0.5->32.0
Turkey | Enterobacter spp. | 51 | 1995 | >32.0 | 0.13->32.0
Turkey | Klebsiella spp. | 100 | 1995 | 1.0 | 0.13-2.0
Turkey | Proteus spp. | 19 | 1995 | 1.0 | 0.06-32.0
Turkey | Pseudomonas spp. [MIC50 is 32 μg/mL] | 31 | 1995 | >32.0 | 0.06->32.0
Turkey | Salmonella spp. | 24 | 1995 | 1.0 | 0.5-1.0
Turkey | Staphylococcus spp. (coagulase positive) | 17 | 1995 | 2.0 | 1.0-2.0
Turkey | Staphylococcus spp. (coagulase negative) | 26 | 1995 | 8.0 | 0.13->32.0
Chicken | Escherichia coli | 62 | 1997-1998 | 0.50 | 0.25-2.0
Chicken | Escherichia coli | 53 | 1998-1999 | 4.0 | 0.25->4.0
Chicken | Escherichia coli | 67 | 1999-2000 | 0.50 | 0.12-16.0
Chicken | Escherichia coli | 90 | 2000-2001 | 1.0 | ≤ 0.03-8.0

Based on the pharmacokinetic studies of ceftiofur in swine and cattle after a single intramuscular injection of 1.36 to 2.27 mg ceftiofur equivalents/lb (3.0 to 5.0 mg/kg) BW (swine) or 0.5 to 1.0 mg ceftiofur equivalents/lb (1.1 to 2.2 mg/kg) BW (cattle) and the MIC and disk (30 μg) diffusion data, the following breakpoints are recommended by CLSI.

Zone Diameter (mm) | MIC (μg/mL) | Interpretation
≥ 21 | ≤ 2.0 | (S) Susceptible
18-20 | 4.0 | (I) Intermediate
≤ 17 | ≥ 8.0 | (R) Resistant

A report of "Susceptible" indicates that the pathogen is likely to be inhibited by generally achievable blood levels. A report of "Intermediate" is a technical buffer zone and isolates falling into this category should be retested. Alternatively the organism may be successfully treated if the infection is in a body site where drug is physiologically concentrated. A report of "Resistant" indicates that the achievable drug concentrations are unlikely to be inhibitory and other therapy should be selected.

Based on the pharmacokinetic studies of ceftiofur in horses after a single intramuscular injection of 1 mg ceftiofur equivalents/lb (2.2 mg/kg) BW, clinical effectiveness data and MIC data, the following breakpoint is recommended by CLSI.

Zone Diameter (mm) | MIC (μg/mL) | Interpretation
≥ 22 | ≤ 0.25 | (S) Susceptible

The susceptible only category is used for populations of organisms (usually one species) for which regression analysis (disk vs. MIC) cannot be performed. These breakpoints will permit detection of strains with decreased susceptibility as compared to the original population.

Standardized procedures [Clinical and Laboratory Standards Institute (CLSI). Performance Standards for Antimicrobial Disk and Dilution Susceptibility Tests for Bacteria Isolated from Animals; Approved Standard – Second Edition. NCCLS document M31-A2. CLSI, 940 West Valley Road, Suite 1400, Wayne, Pennsylvania 19087-1898, 2002.] require the use of laboratory control organisms for both standardized diffusion techniques and standardized dilution techniques. The 30 μg ceftiofur sodium disk should give the following zone diameters and the ceftiofur sodium standard reference powder (or disk) should provide the following MIC values for the reference strain. Ceftiofur sodium disks or powder reference standard is appropriate for both ceftiofur salts.

Table 3. Acceptable quality control ranges for ceftiofur against Clinical and Laboratory Standards Institute recommended American Type Culture Collection (ATCC) reference strains
Organism Name (ATCC Number) | Zone Diameter [All testing performed using a 30μg disk.] (mm) | MIC Range (μg/mL)
Escherichia coli (25922) | 26–31 | 0.25–1.0
Staphylococcus aureus (29213) | — | 0.25–1.0
Staphylococcus aureus (25923) | 27–31 | —
Pseudomonas aeruginosa (27853) | 14–18 | 16.0–64.0
Actinobacillus pleuropneumoniae (27090) | 34–42 [Quality control ranges are applicable only to tests performed by disk diffusion test using a chocolate Mueller-Hinton agar, incubated in 5-7% CO2 for 20-24 hours.] | 0.004–0.015 [MIC quality control ranges are applicable only to tests performed by broth microdilution procedures using veterinary fastidious medium (VFM).]
Histophilus somni (700025) | 36–46 | 0.0005–0.004

ANIMAL SAFETY

Cattle

Results from a five-day tolerance study in normal feeder calves indicated that formulated ceftiofur was well tolerated at 25 times (25 mg/lb/day) the highest recommended dose of 1.0 mg/lb/day for five consecutive days. Ceftiofur administered intramuscularly had no adverse systemic effects.

In a 15-day safety/toxicity study, five steer and five heifer calves per group were intramuscularly administered formulated ceftiofur at 0 (vehicle control), 1, 3, 5 and 10 times the highest recommended dose of 1.0 mg/lb/day to determine the safety factor. There were no adverse systemic effects indicating that the formulated ceftiofur has a wide margin of safety when injected intramuscularly into the feeder calves at 10 times (10 mg/lb/day) the recommended dose for three times (15 days) the recommended three to five days of therapy. The formulation was shown to be a slight muscle irritant based on results of histopathological evaluation of the injection sites at 1 and 3 times the highest recommended dose of 1.0 mg/lb/day. The histopathological evaluations were conducted at posttreatment days 1, 3, 7 and 14.

The injection of NAXCEL Sterile Powder at the recommended dose administered SC in the neck of cattle was well tolerated. However, a several square centimeter area of yellow-red discoloration resulting from a single SC injection persisted in many of the cattle beyond 4.5 days post-injection. Also, one of the animals developed an abscess at the injection site.

Swine

Results from a five-day tolerance study in normal feeder pigs indicated that formulated ceftiofur was well tolerated when administered at 57 mg/lb (more than 25 times the highest recommended daily dosage of 2.27 mg/lb of body weight) for five consecutive days. Ceftiofur administered intramuscularly to pigs produced no overt adverse signs of toxicity.

To determine the safety factor and to measure the muscle irritancy potential in swine, a safety/toxicity study was conducted. Five barrows and five gilts per group were intramuscularly administered formulated ceftiofur at 0, 2.27, 6.81 and 11.36 mg/lb of body weight for 15 days which is 0, 1, 3 and 5 times the highest recommended dose of 2.27 mg/lb of body weight/day and 5 times the recommended treatment length of 3 days. There were no adverse systemic effects indicating that formulated ceftiofur has a wide margin of safety when injected intramuscularly into feeder pigs at the highest recommended dose of 2.27 mg/lb/day for 3 days or at levels up to 5 times the highest recommended dose for 5 times the recommended length of treatment. The formulation was shown to be a slight muscle irritant based on results of histopathological evaluation of the injection sites at posttreatment days 1, 2, 3 and 4. By day 10 post injection the muscle reaction was subsiding and at day 15 post injection there was little evidence of muscle damage in any of the pigs in any of the treatment groups.

Sheep

In a 15-day safety/toxicity study in sheep, three wether and three ewe lambs per group were given formulated ceftiofur sodium by the intramuscular route 0 (sterile water vehicle), 1, 3 or 5 times the recommended dose of 1.0 mg/lb/day for 3 times the recommended maximum duration of 5 days of treatment. There were no adverse systemic effects indicating that formulated ceftiofur is well tolerated and has a wide margin of safety in sheep. Based on examination of injection sites from study days 9, 11, 13 and 15, a low incidence of visual changes and histopathologic findings of mild, reversible inflammation from all groups including the controls indicated that the formulation is a slight muscle irritant.

Goats

In a 15-day safety/toxicity study 5 lactating does, 5 dry does, and 5 wethers were given formulated ceftiofur by the intramuscular route with 11 mg/kg/day for 15 days. This constitutes 5 times the recommended dose for 3 times the recommended maximum duration of 5 days of treatment. There were no adverse systemic effects indicating that formulated ceftiofur is well tolerated and has a wide margin of safety in goats.

Horses

In a safety study, horses received a daily intramuscular injection of either 0 mg/lb/day (saline control), 1.0 mg/lb/day (50 mg/mL), 3.0 mg/lb/day (100 mg/mL), or 5.0 mg/lb/day (200 mg/mL) of an aqueous solution of ceftiofur sodium for 30 or 31 days. Ceftiofur sodium was well tolerated when administered intramuscularly to male and female horses at doses up to 5.0 mg/lb/day for 30 or 31 days. No clinical evidence of irritation was noted at any dose. The drug-related changes detected in this study were limited to a transient decrease in food consumption in horses receiving 3.0 or 5.0 mg/lb/day ceftiofur, and general mild skeletal muscle irritation at the injection sites which resolved by regeneration of muscle fibers.

In a tolerance study, horses received a single daily intravenous infusion of either 0 (saline), 10.0 or 25.0 mg/lb/day of an aqueous solution (50 mg/mL) of ceftiofur for 10 days. The results indicated that ceftiofur administered intravenously at a dose of 10.0 or 25.0 mg/lb/day apparently can change the bacterial flora of the large intestine thereby leading to inflammation of the large intestine with subsequent diarrhea and other clinical signs (loose feces, eating bedding straw, dehydration, rolling or colic and a dull, inactive demeanor). Decreased food consumption, a loss of body weight, hematologic changes related to acute inflammation and stress, and serum chemistry changes related to decreased food consumption and diarrhea were also associated with treatment at these doses. The adverse effects were most severe a few days after dosing was initiated and tended to become less severe toward the end of the 10-day dosing period.

Dogs

Ceftiofur sodium was well tolerated at the therapeutic dose and is safe for the treatment of urinary tract infections in dogs. In the acute safety study, ceftiofur was well tolerated by dogs at the recommended level (1.0 mg/lb) for 5-14 days. When administered subcutaneously for 42 consecutive days, one of four females developed thrombocytopenia (15 days) and anemia (36 days). Thrombocytopenia and anemia also occurred at the 3× and 5× dose levels.

In the reversibility phase of the study (5× dose), the thrombocytopenia reversed within 8 days, and of the two anemic animals the male recovered within 6 weeks and the female was sacrificed due to the severity of the anemia. In the 15-day tolerance study in dogs, high subcutaneous doses (25 and 125 times the recommended therapeutic dose) produced a progressive and dose-related thrombocytopenia, with some dogs also exhibiting anemia and bone marrow changes. The hematopoietic changes noted in dogs treated with ceftiofur were similar to those associated with long-term cephalosporin administration in dogs and also man. The hematopoietic effects are not expected to occur as a result of recommended therapy.

Day-Old Chicks

In an acute toxicity study of ceftiofur in day-old chicks, a total of 60 male and 60 female chicks were each given single subcutaneous injections of 10, 100 or 1,000 mg/kg of body weight. Treatment on day 1 was followed by 6 days of observation; body weight was determined on days 1, 4 and 7; and selected hematology parameters were evaluated on day 4. No meaningful differences were noted among the treated and control groups of chicks for the parameters evaluated. Histopathologic evaluation of all deaths and chicks surviving to termination did not reveal a target organ or tissue of potential toxicity of ceftiofur when administered at up to 20 times (100 mg/kg) the intended highest use dosage.

Day-Old Turkey Poults

In an acute toxicity study of ceftiofur in day-old turkey poults, a total of 30 male and 30 female poults were each administered single subcutaneous injections of 100, 400 or 800 mg/kg body weight. Injection on day 1 was followed by 6 days of observation; body weight on days 1, 4, and 7; and selected hematology parameters on day 4. No meaningful differences were noted between the treated groups at 100 or 400 mg ceftiofur/kg and a negative control group for the parameters evaluated. Histopathologic evaluation of all deaths and poults surviving to termination did not reveal a target organ or tissue of potential toxicity of ceftiofur when administered at up to 50 times (400 mg/kg) the highest use dosage. A dose of 800 mg/kg (100 times the intended highest use dosage) was toxic, resulting in clinical signs and deaths accompanied by gross and microscopic morphologic tissue alterations.

TISSUE RESIDUE DEPLETION

Cattle

A radiolabeled residue metabolism study established tolerances for ceftiofur residues in cattle kidney, liver and muscle. These tolerances of ceftiofur residues are 0.4 ppm in kidney, 2.0 ppm in liver, 1.0 ppm in muscle, and 0.1 ppm in milk.

A pivotal tissue residue decline study was conducted in cattle. In this study, cattle received an intramuscular injection of 1.0 mg of ceftiofur per lb body weight (2.2 mg of ceftiofur per kg body weight) for five consecutive days. Ceftiofur residues in tissues were less than the tolerances for ceftiofur residues in tissues such as kidney, liver and muscle by 4 days after dosing. These data collectively support a 4-day pre-slaughter withdrawal period in cattle when used according to label directions.

Swine

Radiolabeled residue metabolism studies established tolerances for ceftiofur residues in swine kidney, liver, and muscle. These tolerances of ceftiofur residues are 0.25 ppm in kidney, 3.0 ppm in liver and 2.0 ppm in muscle.

A pivotal tissue residue decline study was conducted in swine. In this study, pigs received 2.27 mg of ceftiofur per lb body weight (5 mg of ceftiofur per kg body weight) per day for three consecutive days. Ceftiofur residues in tissues were less than the tolerances for ceftiofur residues in tissues such as kidney, liver and muscle by 4 days after dosing. These data collectively support a 4-day pre-slaughter withdrawal period in swine when used according to label directions.

STORAGE CONDITIONS

Store unreconstituted product at controlled room temperature 20° to 25° C (68° to 77° F).

Store reconstituted product either in a refrigerator 2° to 8° C (36° to 46° F) for up to 7 days or at controlled room temperature 20° to 25° C (68° to 77° F) for up to 12 hours.

Protect from light. Color of the cake may vary from off-white to a tan color. Color does not affect potency.

ONE-TIME SALVAGE PROCEDURE FOR RECONSTITUTED PRODUCT

At the end of the 7-day refrigeration or 12-hour room temperature storage period following reconstitution, any remaining reconstituted product may be frozen for up to 8 weeks without loss in potency or other chemical properties. This is a one-time only salvage procedure for the remaining product. To use this salvaged product at any time during the 8-week storage period, hold the vial under warm running water, gently swirling the container to accelerate thawing, or allow the frozen material to thaw at room temperature. Rapid freezing or thawing may result in vial breakage. Any product not used immediately upon thawing should be discarded.

HOW SUPPLIED

NAXCEL Sterile Powder is available in the following package sizes:

- 1 gram vial
- 4 gram vial

Approved by FDA under NADA # 140-338
zoetis
Distributed by:
Zoetis Inc.
Kalamazoo, MI 49007
Revised: May 2022
40039129

PRINCIPAL DISPLAY PANEL - 1 g 12 Vial Carton

40039131

PRINCIPAL DISPLAY PANEL - 4 g 6 Vial Carton

40039153